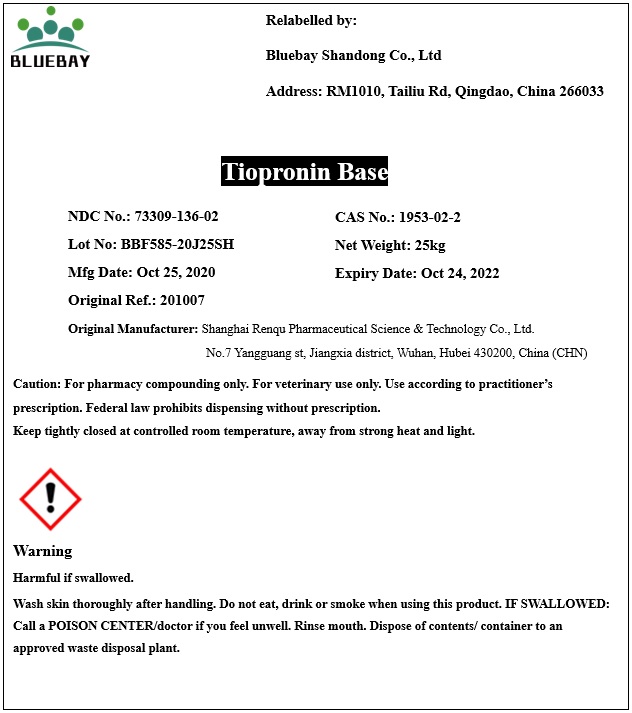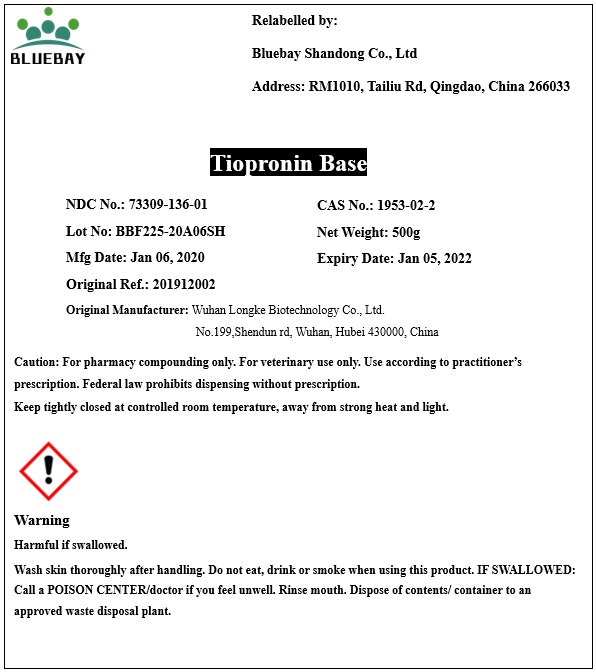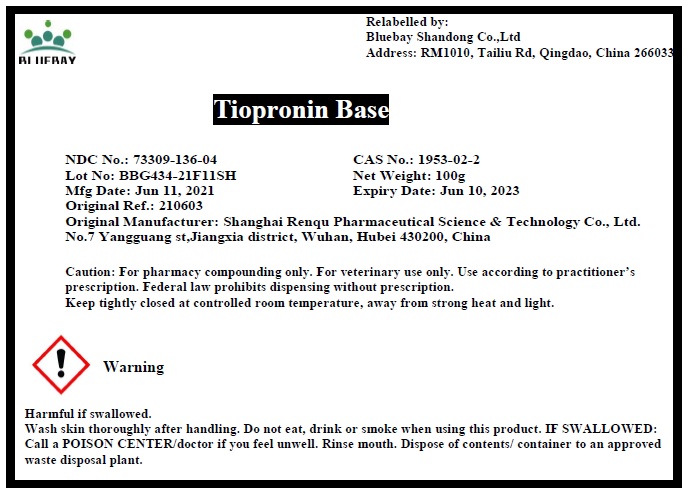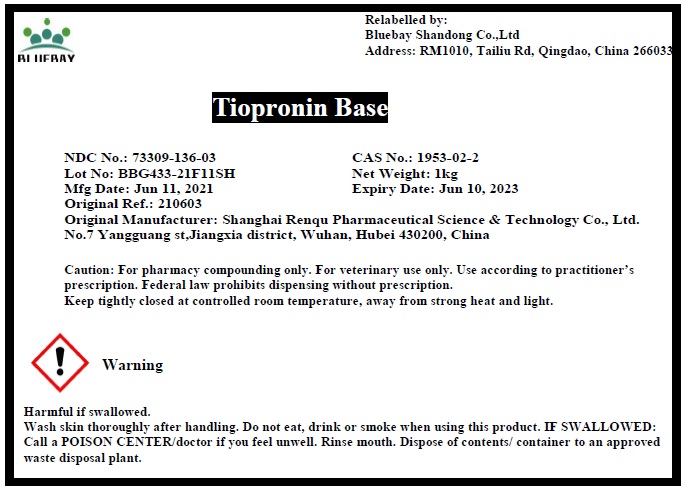 DRUG LABEL: Tiopronin Base
NDC: 73309-136 | Form: POWDER
Manufacturer: BLUEBAY SHANDONG CO.,LTD
Category: other | Type: BULK INGREDIENT
Date: 20210823

ACTIVE INGREDIENTS: TIOPRONIN 1 g/1 g

Tiopronin Base